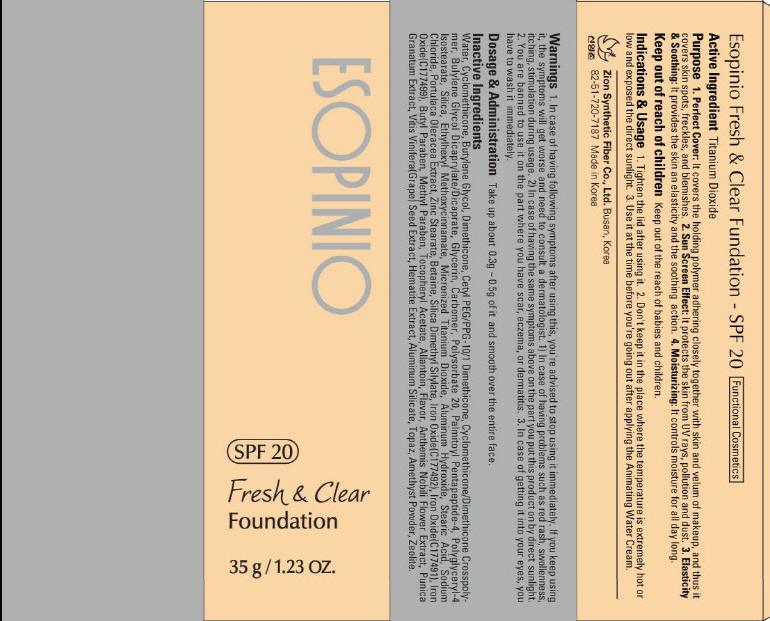 DRUG LABEL: ESOPINIO FRESH AND CLEAR FOUNDATION
NDC: 44781-140 | Form: CREAM
Manufacturer: ZION SYNTHETIC FIBER CO., LTD.
Category: otc | Type: HUMAN OTC DRUG LABEL
Date: 20110829

ACTIVE INGREDIENTS: TITANIUM DIOXIDE 3.5 g/35 g
INACTIVE INGREDIENTS: Water; Cyclomethicone; Butylene Glycol; Dimethicone; Glycerin; CARBOMER 934; POLYSORBATE 20; SILICON DIOXIDE; OCTINOXATE; STEARIC ACID; ALUMINUM HYDROXIDE; SODIUM CHLORIDE; ZINC STEARATE; BETAINE; BUTYLPARABEN; METHYLPARABEN; ALLANTOIN; CHAMAEMELUM NOBILE; WINE GRAPE; ALUMINUM SILICATE

Drug Facts

Active ingredient: TITANIUM DIOXIDE

Inactive ingredients:

Water, Cyclomethicone, Butylene Glycol, Dimethicone, Cetyl PEG/PPG-10/1 Dimethicone, Cyclomethicone/Dimethicone Crosspolymer, Butylene Glycol Dicaprylate/Dicaprate, Glycerin, Carbomer, Polysorbate 20, Palmitoyl Pentapeptide-4, Polyglyceryl-4-Isostearate, Silica, Ethylhexyl Methoxycinnamate, Micronized Titanium Dioxide Aluminum Hydroxide Stearic Acid, Sodium Chloride, Portulaca Oleracea Extract, Zinc Stearate, Betaine, Silica Dimethyl Silylate, Iron Oxide, Butyl Paraben, Methyl Paraben, Tocopheryl Acetate, Allantoin, Flavor, Anthemis Nobilis Flower Extract, Punica Granatum Extract, Vitis Vinifera(Grape) Seed Extract, Hematite Extract, Aluminum Silicate, Topaz, Amethyst Powder, Zeolite

PURPOSE

Purpose: It protects the skin from UV rays, pollution and dust.

Warnings:
In case of having following symptoms after using this, you're advised to stop using it immediately. If you keep using it, the symptoms will get worse and need to consult a dermatologist.
- In case of having problems such as red rash, swollenness, itching, stimulation during usage.
- In case of having the same symptoms above on the part you put this product on by direct sunlight.
You are banned to use it on the part where you have a scar, eczema, or dermatitis.
In case of getting it into your eyes, you have to wash it immediately.

Keep out of reach of children:

Keep out of the reach of babies and children.

Indications and usage:
Tighten the lid after using it.
Don't keep it in the place where the temperature is extremely hot or low and exposed the direct sunlight.
Use it at the time before you're going out after applying the Animating Water Cream.

Dosage and administration:
Take up about 0.3g - 0.5g of it and smooth over the entire face.